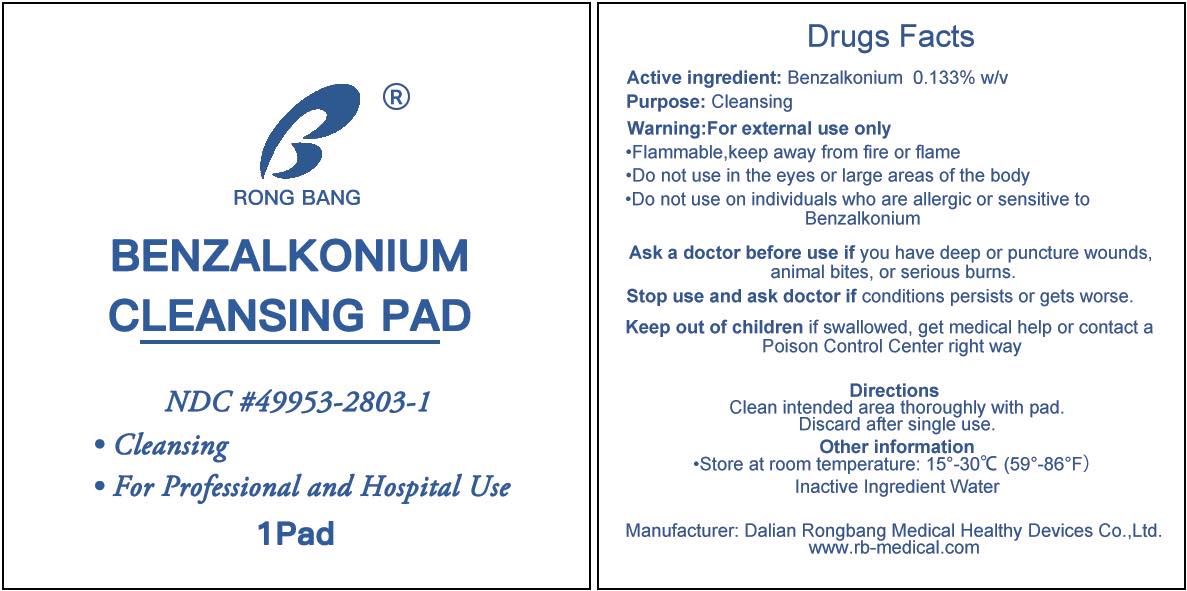 DRUG LABEL: Rongbang BZK Cleansing Pad
NDC: 49953-2803 | Form: SWAB
Manufacturer: Dalian Rongbang Medical Healthy Devices Co., Ltd.
Category: otc | Type: HUMAN OTC DRUG LABEL
Date: 20231228

ACTIVE INGREDIENTS: BENZALKONIUM CHLORIDE 0.133 mg/100 g
INACTIVE INGREDIENTS: WATER

Rongbang Benzalkonium Cleansing Pad

ACTIVE INGREDIENT

Benzalkonium 0.133% w/v

Purpose: Cleansing

Warning:

For external use only

·Flammable,keep away from fire or flame

Do not Use

·With electrocautery procedures

·Do not use in the eyes

·Do not use on individuals who are allergic or sensitive to Benzalkonium

Ask a doctor before use if you have deep or puncture wounds, animal bites, or serious burns.

Stop use and ask doctor if conditions persists or gets worse.

KEEP OUT OF REACH OF CHILDREN

Keep out of children if swallowed, get medical help or contact a Poison Control Center right way

DIRECTIONS

- Clean intended area thoroughly with pad.
- Discard after single use.

OTHER INFORMATION

Store at room temperature: 15°-30℃ (59°-86°F）

QUESTIONS

Manufacturer : Dalian Rongbang Medical Healthy Devices Co.,Ltd.

www.rb-medical.com

INDICATIONS AND USAGE

Used for cleansing

INACTIVE INGREDIENT

Water